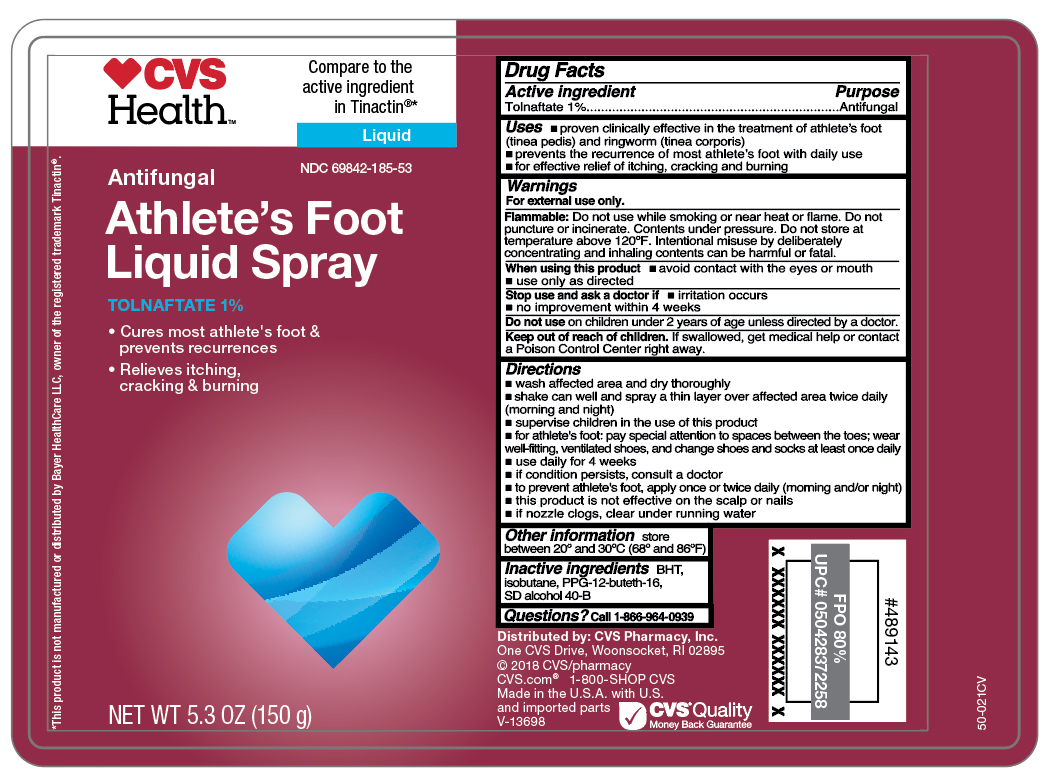 DRUG LABEL: Tolnaftate
NDC: 69842-185 | Form: AEROSOL, SPRAY
Manufacturer: CVS Pharmacy
Category: otc | Type: HUMAN OTC DRUG LABEL
Date: 20260218

ACTIVE INGREDIENTS: TOLNAFTATE 1.5 g/150 g
INACTIVE INGREDIENTS: BHT; ISOBUTANE; PPG-12-BUTETH-16; ALCOHOL

CVS Antifungal Tolnaftate Liquid Spray

Active ingredient

Tolnaftate 1%

Purpose

Antifungal

Uses

- proven clinically effective in the treatment of athlete's foot (tinea pedis) and ringworm (tinea corporis)
- prevent recurrence of most athlete's foot with daily use
- for effective relief of itching, cracking and burning

Warnings

For external use only.

Flammable:

Do not use while smoking or near heat or flame. Do not puncture or incinerate. Contents under pressure. Do not store at temperature above 120ºF. Intentional misuse by delibrately concentrating and inhaling contents can be harmful or fatal.

When using this product

- avoid contact with the eyes or mouth
- use only as directed

Stop use and ask a doctor if

- irritation occurs
- no improvement within 4 weeks

Do not use

on children under 2 years of age unless directed by a doctor.

Keep out of reach of children.

If swallowed, get medical help or contact a Poison Control Center right away.

Directions

- wash affected area and dry thoroughly
- shake can well and spray a thin layer over affected area twice daily (morning and night)
- supervise children in the use of this product
- for athlete's foot, pay special attention to spaces between the toes, wear well-fitting, ventilated shoes and change shoes and socks at least once daily
- use daily for 4 weeks
- if conditions persist, consult a doctor
- to prevent athlete's foot, apply once or twice daily (moming and/or night)
- this product is not effective on the scalp or nails
- if nozzle clogs, clear under running water

Other information

store between 20º and 30ºC (68ºF and 86º)

Inactive ingredients

BHT, isobutane, PPG-12-buteth-16, SD alcohol 40-B

Questions?

call 1-866-964-0939

Principal Display Panel

CVS

Health

Antifungal

Athlete's Foot

Liquid Spray

TOLNAFTATE 1%

- Cures most athlete's foot &

prevents recurrences

- Relieves itching,

cracking & burning

NET WT 5.3 OZ (150g)